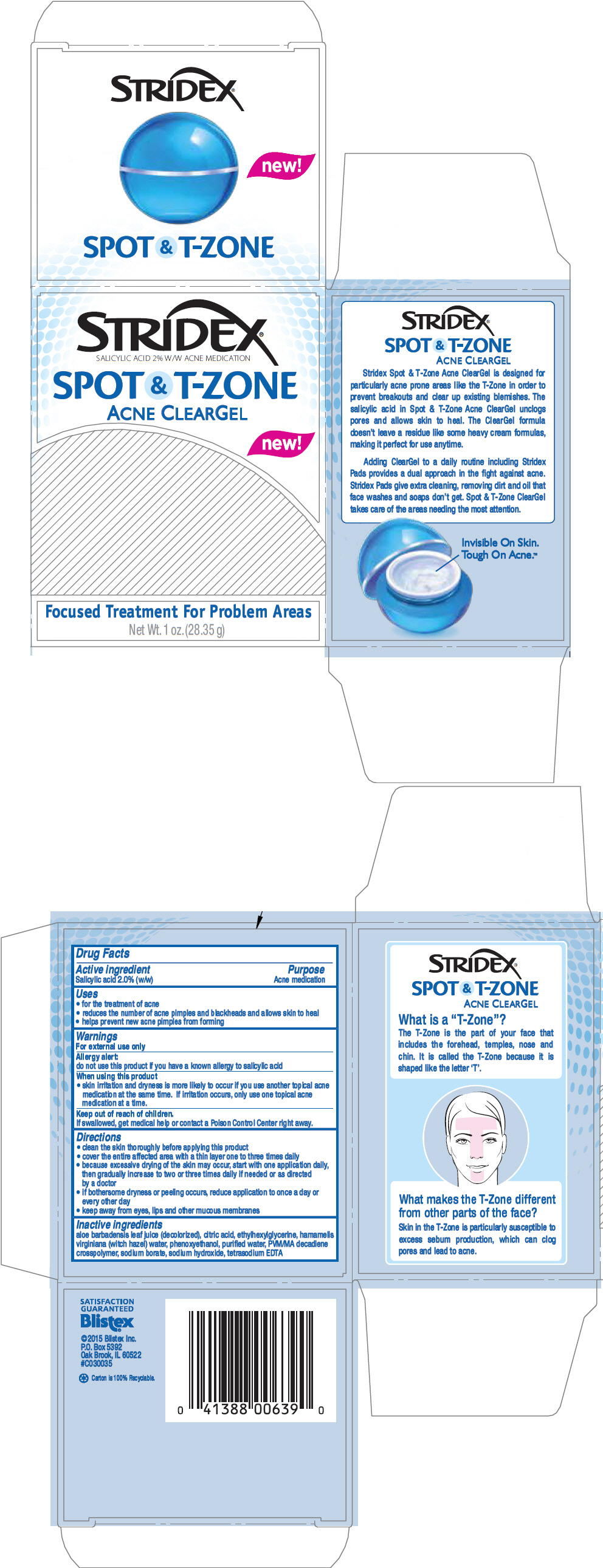 DRUG LABEL: Blistex Stridex Spot and T-Zone Acne ClearGel
NDC: 10157-2101 | Form: GEL
Manufacturer: Blistex Inc
Category: otc | Type: HUMAN OTC DRUG LABEL
Date: 20151124

ACTIVE INGREDIENTS: Salicylic Acid 2 g/100 g
INACTIVE INGREDIENTS: WATER; HAMAMELIS VIRGINIANA TOP WATER; SODIUM BORATE; SODIUM HYDROXIDE; PHENOXYETHANOL; EDETATE SODIUM; ETHYLHEXYLGLYCERIN; CITRIC ACID MONOHYDRATE; ALOE VERA LEAF; MALEIC ANHYDRIDE; 1,9-DECADIENE; METHYL VINYL ETHER

Blistex® Stridex® Spot and T-Zone Acne ClearGel

Drug Facts

Active ingredient

Salicylic acid 2.0% (w/w)

Purpose

Acne medication

Uses

- for the treatment of acne
- reduces the number of acne pimples and blackheads and allows skin to heal
- helps prevent new acne pimples from forming

Warnings

For external use only

Allergy alert:

do not use this product if you have a known allergy to salicylic acid

When using this product

- skin irritation and dryness is more likely to occur if you use another topical acne medication at the same time. If irritation occurs, only use one topical acne medication at a time.

Keep out of reach of children.

If swallowed, get medical help or contact a Poison Control Center right away.

Directions

- clean the skin thoroughly before applying this product
- cover the entire affected area with a thin layer one to three times daily
- because excessive drying of the skin may occur, start with one application daily, then gradually increase to two or three times daily if needed or as directed by a doctor
- if bothersome dryness or peeling occurs, reduce application to once a day or every other day
- keep away from eyes, lips and other mucous membranes

Inactive ingredients

aloe barbadensis leaf juice (decolorized), citric acid, ethylhexylglycerine, hamamelis virginiana (witch hazel) water, phenoxyethanol, purified water, PVM/MA decadiene crosspolymer, sodium borate, sodium hydroxide, tetrasodium EDTA

PRINCIPAL DISPLAY PANEL - 28.35 g Jar Carton

STRIDEX®
SALICYLIC ACID 2% W/W ACNE MEDICATION

SPOT & T-ZONE
ACNE CLEARGEL

new!

Focused Treatment For Problem Areas

Net Wt. 1 oz. (28.35 g)